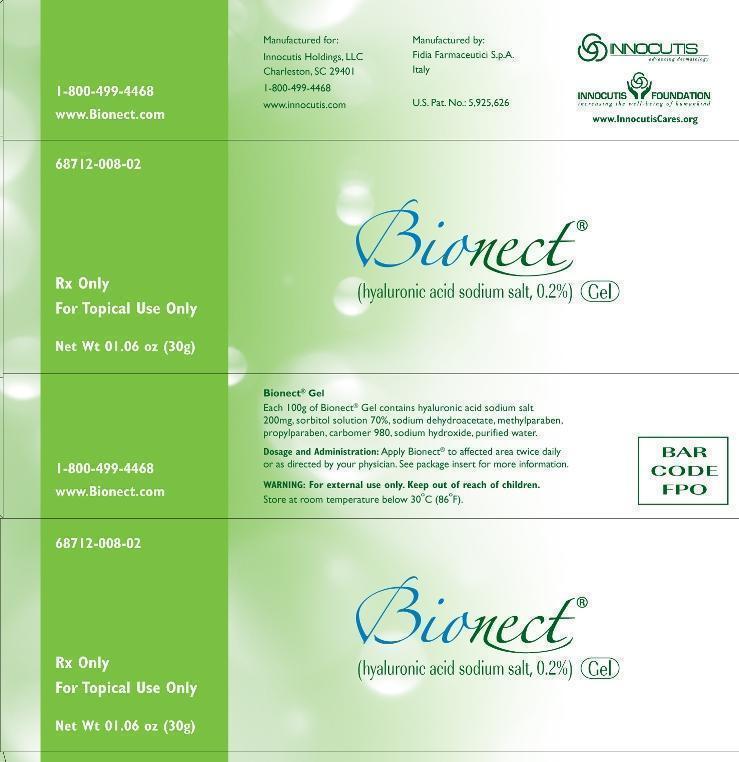 DRUG LABEL: Bionect Gel
NDC: 68712-008
Manufacturer: Innocutis Holdings LLC
Category: other | Type: PRESCRIPTION MEDICAL DEVICE LABEL
Date: 20141007
INACTIVE INGREDIENTS: WATER; METHYLPARABEN; PROPYLPARABEN; SORBITOL; SODIUM DEHYDROACETATE; CARBOMER 940; SODIUM HYDROXIDE

Bionect Gel (hyaluronic acid sodium salt, 0.2%)

Description:

Bionect Gel is a clear, colorless gel. The principal component is the sodium salt of hyaluronic acid (0.2%). The sodium hyaluronate (Hyalastine) is derived from a natural fermentation process. Hyaluronic acid is a biological polysaccharide (glycosaminoglycan) and is a major component of the extracellular matric of the connective tissues.

Indications:

Bionect is indicated for the dressing and management of partial to full thickness dermal ulcers (pressure sores, venous stasis ulcers, arterial ulcers, diabetic ulcers), wounds including cuts, abrasions, donor sites, and post-operative incisions, irritations of the skin, and first and second degree burns, The dressing is intended to cover a wound or burn on a patient's skin, and protect against abrasion, friction and desiccation.

Directions:

The wounds or ulcers should be cleaned and disinfected prior to treatment. In the event of long-standing ulcers, it may be advisable to clean and/or to debride the wound by surgical or enzymatic means, prior to treatment. Apply a thin layer of Bionect without extensive rubbing onto the wound surface, two or three times per day. Cover the lesion area with a sterile gauze pad and, if necessary, with an elastic or compressive bandage.

Warnings:

If conditions worsens, consult your physician immediately. Keep this product out of the reach of children. The prolonged use of the product may give rise to sensitization phenomena. Should this happen, discontinue the treatment and follow a suitable therapy. Do not use the product after expiration date reported on the package.

Ingredients:

Hyaluronic acid sodium salt, sorbitol solution 70%, sodium dehydroacetate, methylparaben, propylparaben, carbomer 980, sodium hydroxide, purified water.

Contraindications:

Do not administer to patients with known hypersensitivity to this product.

Interactions:

Do not use concomitantly with disinfectants containing quaternary ammonium salts because hyaluronic acid can precipitate in their presence. The concomitant topical treatment of wounds with antibiotics or other local agents has never given rise to interactions or incompatibilities with Bionect.

Precautions:

Avoid direct contact of container with the affected area. Each container of Bionect should be used by one patient only in order to reduce the risk of cross infection.

Warning

Bionect Gel - Protect from freezing. Keep out of reach of children

Adverse Reactions:

All suspected adverse reactions occurring during the treatment with Bionect should be report to your doctor.

How Supplied:

Bionect Gel is supplied in a 30g tube 68712-008-02, 60g tube 68712-008-03 and 100g tube 68712-008-04

Storage:

Please store Bionect at room temperature. Bionect Gel may be stored for up to 24 months under these conditions. Store at room temperature below 86F (30C).

Manufactured by: Fidia Farmaceutici S.p.A - Italy

Distributed by: Innocutis Holdings, LLC

Charleston SC 29401

800-499-4468

www.innocutis.com

www.bionect.com

U.S. Pat. No.: 5,925,626